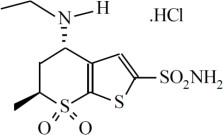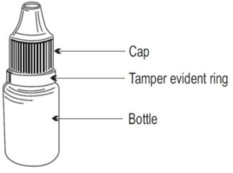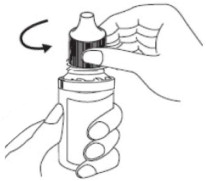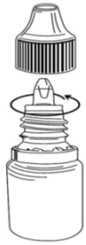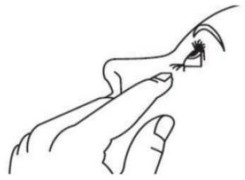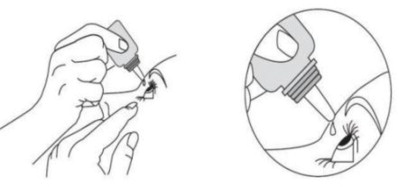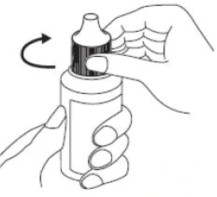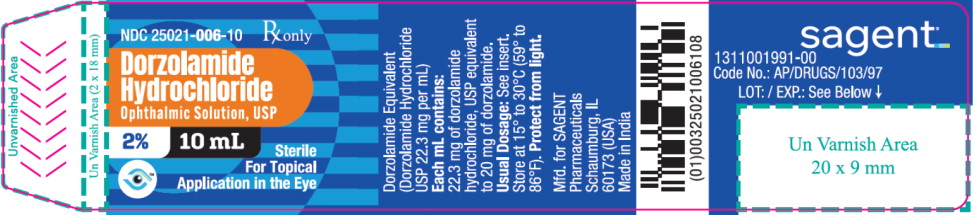 DRUG LABEL: Dorzolamide Hydrochloride
NDC: 25021-006 | Form: SOLUTION/ DROPS
Manufacturer: Sagent Pharmaceuticals
Category: prescription | Type: HUMAN PRESCRIPTION DRUG LABEL
Date: 20260109

ACTIVE INGREDIENTS: Dorzolamide Hydrochloride 20 mg/1 mL
INACTIVE INGREDIENTS: Hydroxyethyl Cellulose (2000 MPA.S at 1%); Mannitol; Trisodium Citrate Dihydrate; Sodium Hydroxide; Water; Benzalkonium Chloride

HIGHLIGHTS OF PRESCRIBING INFORMATION

These highlights do not include all the information needed to use DORZOLAMIDE HYDROCHLORIDE OPHTHALMIC SOLUTION safely and effectively. See full prescribing information for DORZOLAMIDE HYDROCHLORIDE OPHTHALMIC SOLUTION.
DORZOLAMIDE HYDROCHLORIDE ophthalmic solution 2%, for topical ophthalmic use
Initial U.S. Approval: 1994

1 INDICATIONS AND USAGE

Dorzolamide Hydrochloride Ophthalmic Solution is a carbonic anhydrase inhibitor indicated for the treatment of elevated intraocular pressure in patients with ocular hypertension or open-angle glaucoma. (1)

2 DOSAGE AND ADMINISTRATION

The dose is one drop of Dorzolamide Hydrochloride Ophthalmic Solution in the affected eye(s) three times daily. Dorzolamide Hydrochloride Ophthalmic Solution may be used concomitantly with other topical ophthalmic drug products to lower intraocular pressure. (2)

3 DOSAGE FORMS AND STRENGTHS

Ophthalmic solution containing dorzolamide 2% (20 mg per mL). (3)

4 CONTRAINDICATIONS

Dorzolamide Hydrochloride Ophthalmic Solution is contraindicated in patients who are hypersensitive to any component of this product. (4, 5.1)

5 WARNINGS AND PRECAUTIONS

- Sulfonamide Hypersensitivity (5.1)
- Bacterial Keratitis (5.2)
- Corneal Endothelium (5.3)
- Allergic Reactions (5.4)
- Acute Angle-Closure Glaucoma (5.5)

6 ADVERSE REACTIONS

The most frequently reported adverse reactions associated with Dorzolamide Hydrochloride Ophthalmic Solution were ocular burning, stinging, or discomfort immediately following ocular administration (approximately one-third of patients). Approximately one-quarter of patients noted a bitter taste following administration. Superficial punctate keratitis occurred in 10 to 15% of patients and signs and symptoms of ocular allergic reaction in approximately 10%. (6)

To report SUSPECTED ADVERSE REACTIONS, contact Sagent Pharmaceuticals at 1-866-625-1618 or FDA at 1-800-FDA-1088 or www.fda.gov/medwatch.

7 DRUG INTERACTIONS

Potential additive effect of oral carbonic anhydrase inhibitor with Dorzolamide Hydrochloride Ophthalmic Solution. (7.1)

Potential acid-base and electrolyte disturbances. (7.2)

FULL PRESCRIBING INFORMATION

1 INDICATIONS AND USAGE

Dorzolamide Hydrochloride Ophthalmic Solution is indicated in the treatment of elevated intraocular pressure in patients with ocular hypertension or open-angle glaucoma.

2 DOSAGE AND ADMINISTRATION

The dose is one drop of Dorzolamide Hydrochloride Ophthalmic Solution in the affected eye(s) three times daily.

Dorzolamide Hydrochloride Ophthalmic Solution may be used concomitantly with other topical ophthalmic drug products to lower intraocular pressure. If more than one topical ophthalmic drug is being used, the drugs should be administered at least five minutes apart.

3 DOSAGE FORMS AND STRENGTHS

Ophthalmic solution containing dorzolamide 2% (20 mg per mL) equivalent to 22.3 mg per mL of dorzolamide hydrochloride, USP.

4 CONTRAINDICATIONS

Dorzolamide Hydrochloride Ophthalmic Solution is contraindicated in patients who are hypersensitive to any component of this product [see Warnings and Precautions (5.1)].

5 WARNINGS AND PRECAUTIONS

5.1 Sulfonamide Hypersensitivity

Dorzolamide Hydrochloride Ophthalmic Solution contains dorzolamide, a sulfonamide; and although administered topically, it is absorbed systemically. Therefore, the same types of adverse reactions that are attributable to sulfonamides may occur with topical administration of Dorzolamide Hydrochloride Ophthalmic Solution. Fatalities have occurred, although rarely, due to severe reactions to sulfonamides including Stevens-Johnson syndrome, toxic epidermal necrolysis, fulminant hepatic necrosis, agranulocytosis, aplastic anemia, and other blood dyscrasias. Sensitization may recur when a sulfonamide is readministered irrespective of the route of administration. If signs of serious reactions or hypersensitivity occur, discontinue the use of this preparation [see Contraindications (4)].

5.2 Bacterial Keratitis

There have been reports of bacterial keratitis associated with the use of multiple-dose containers of topical ophthalmic products. These containers had been inadvertently contaminated by patients who, in most cases, had a concurrent corneal disease or a disruption of the ocular epithelial surface.

5.3 Corneal Endothelium

Carbonic anhydrase activity has been observed in both the cytoplasm and around the plasma membranes of the corneal endothelium. There is an increased potential for developing corneal edema in patients with low endothelial cell counts. Caution should be used when prescribing Dorzolamide Hydrochloride Ophthalmic Solution to this group of patients.

5.4 Allergic Reactions

In clinical studies, local ocular adverse effects, primarily conjunctivitis and lid reactions, were reported with chronic administration of Dorzolamide Hydrochloride Ophthalmic Solution. Many of these reactions had the clinical appearance and course of an allergic-type reaction that resolved upon discontinuation of drug therapy. If such reactions are observed, Dorzolamide Hydrochloride Ophthalmic Solution should be discontinued and the patient evaluated before considering restarting the drug [see Adverse Reactions (6)].

5.5 Acute Angle-Closure Glaucoma

The management of patients with acute angle-closure glaucoma requires therapeutic interventions in addition to ocular hypotensive agents.

6 ADVERSE REACTIONS

6.1 Clinical Trials Experience

Because clinical trials are conducted under widely varying conditions, adverse reaction rates observed in the clinical trials of a drug cannot be directly compared to rates in the clinical trials of another drug and may not reflect the rates observed in practice.

Controlled clinical trials: The most frequent adverse reactions associated with Dorzolamide Hydrochloride Ophthalmic Solution were ocular burning, stinging, or discomfort immediately following ocular administration (approximately one-third of patients). Approximately one-quarter of patients noted a bitter taste following administration. Superficial punctate keratitis occurred in 10 to 15% of patients and signs and symptoms of ocular allergic reaction in approximately 10%. Reactions occurring in approximately 1 to 5% of patients were conjunctivitis and lid reactions [see Warnings and Precautions (5.4)], blurred vision, eye redness, tearing, dryness, and photophobia. Other ocular reactions and systemic reactions were reported infrequently, including headache, nausea, asthenia/fatigue; and, rarely, skin rashes, urolithiasis, and iridocyclitis.

In a 3-month, double-masked, active-treatment-controlled, multicenter study in pediatric patients, the adverse reactions profile of Dorzolamide Hydrochloride Ophthalmic Solution was comparable to that seen in adult patients.

6.2 Post-Marketing Experience

The following adverse reactions have been identified during post-approval use of Dorzolamide Hydrochloride Ophthalmic Solution. Because these reactions are reported voluntarily from a population of uncertain size, it is not always possible to reliably estimate their frequency or establish a causal relationship to drug exposure: signs and symptoms of systemic allergic reactions including angioedema, bronchospasm, pruritus, and urticaria; Stevens-Johnson syndrome and toxic epidermal necrolysis; dizziness, paresthesia; ocular pain, transient myopia, choroidal detachment following filtration surgery, eyelid crusting; dyspnea; contact dermatitis, epistaxis, dry mouth and throat irritation.

7 DRUG INTERACTIONS

7.1 Oral Carbonic Anhydrase Inhibitors

There is a potential for an additive effect on the known systemic effects of carbonic anhydrase inhibition in patients receiving an oral carbonic anhydrase inhibitor and Dorzolamide Hydrochloride Ophthalmic Solution. The concomitant administration of Dorzolamide Hydrochloride Ophthalmic Solution and oral carbonic anhydrase inhibitors is not recommended.

7.2 High-Dose Salicylate Therapy

Although acid-base and electrolyte disturbances were not reported in the clinical trials with dorzolamide hydrochloride ophthalmic solution, these disturbances have been reported with oral carbonic anhydrase inhibitors and have, in some instances, resulted in drug interactions (e.g., toxicity associated with high-dose salicylate therapy). Therefore, the potential for such drug interactions should be considered in patients receiving Dorzolamide Hydrochloride Ophthalmic Solution.

8 USE IN SPECIFIC POPULATIONS

8.1 Pregnancy

Risk Summary

There are no adequate and well-controlled studies in pregnant women with Dorzolamide Hydrochloride Ophthalmic Solution. Dorzolamide caused fetal vertebral malformations when administered orally to rabbits at 2.5 mg/kg/day (37 times the clinical exposure). Dorzolamide administered during the period of organogenesis was not teratogenic in rabbits dosed up to 1 mg/kg/day (15 times the clinical exposure). Dorzolamide hydrochloride administered orally to rats during late gestation and lactation caused growth delays in offspring at 7.5 mg/kg/day (52 times the clinical exposure). Growth was not delayed at 1 mg/kg/day (8.0 times the clinical exposure).

The background risk of major birth defects and miscarriage for the indicated population is unknown. In the U.S. general population, the estimated background risk of major birth defects and miscarriage in clinically recognized pregnancies is 2 to 4% and 15 to 20%, respectively.

Data

Animal Data

Developmental toxicity studies were conducted in pregnant rabbits administered dorzolamide hydrochloride orally during the period of organogenesis from gestation days 6 through 18 at doses of 0.2, 1, 2.5, 5, and 10 mg/kg/day. The developmental lowest observed adverse effect level (LOAEL) was 2.5 mg/kg/day, based on vertebral malformations and decreased fetal body weight. The maternal LOAEL was 2.5 mg/kg/day, based on metabolic acidosis and reduced weight gain. The maternal and developmental no adverse effect levels (NOAELs) were 1 mg/kg/day. The rabbit doses of 1 and 2.5 mg/kg/day represent estimated plasma Cmax levels in rabbits 15 and 37 times higher than the lower limit of detection in human plasma following ocular administration, respectively.

Dorzolamide hydrochloride was administered orally to rats during late gestation and lactation (gestation day 17 through postpartum day 20) at doses of 0.1, 1, or 7.5 mg/kg/day. The developmental LOAEL was 7.5 mg/kg/day, based on reduced birth weight, reduced weight gain, and a slight delay in postnatal development (incisor eruption, vaginal canalization and eye openings) secondary to lower offspring body weight. This 7.5 mg/kg/day dose represents an estimated plasma Cmax level in rats 52 times higher than the lower limit of detection in human plasma following ocular administration. The developmental NOAEL was 1 mg/kg/day. The maternal LOAEL was 1 mg/kg/day, based on reduced body weight gain. The maternal NOAEL was 0.1 mg/kg/day. The rat doses of 1 and 0.1 mg/kg/day represent estimated plasma Cmax levels in rats approximately 8.0 times and approximately equal (1x), respectively to the lower limit of detection in human plasma following ocular administration.

8.2 Lactation

Risk Summary

There are no data on the presence of Dorzolamide Hydrochloride Ophthalmic Solution in human milk, the effects on the breastfed infant, or the effects on milk production. The developmental and health benefits of breastfeeding should be considered along with the mother's clinical need for Dorzolamide Hydrochloride Ophthalmic Solution and any potential adverse effects on the breast-fed child from Dorzolamide Hydrochloride Ophthalmic Solution. Dorzolamide is present in the milk of lactating rats (see Data).

Data

Animal Data

Lactating rats were dosed orally with 7.5 mg/kg/day of dorzolamide hydrochloride; dorzolamide and the N-desethyl metabolite were detected in the milk.

8.4 Pediatric Use

Safety and effectiveness of Dorzolamide Hydrochloride Ophthalmic Solution have been demonstrated in pediatric patients in a 3-month, multicenter, double-masked, active-treatment-controlled trial.

8.5 Geriatric Use

No overall differences in safety or effectiveness have been observed between elderly and younger patients.

8.6 Renal and Hepatic Impairment

Dorzolamide has not been studied in patients with severe renal impairment (CrCl < 30 mL/min). Because dorzolamide and its metabolite are excreted predominantly by the kidney, Dorzolamide Hydrochloride Ophthalmic Solution is not recommended in such patients.

Dorzolamide has not been studied in patients with hepatic impairment and should therefore be used with caution in such patients.

10 OVERDOSAGE

Electrolyte imbalance, development of an acidotic state, and possible central nervous system effects may occur. Serum electrolyte levels (particularly potassium) and blood pH levels should be monitored.

11 DESCRIPTION

Dorzolamide Hydrochloride Ophthalmic Solution, USP is a carbonic anhydrase inhibitor formulated for topical ophthalmic use.

Dorzolamide hydrochloride, USP is described chemically as: (4S-trans)-4-(ethylamino)-5,6-dihydro-6-methyl-4H-thieno[2,3-b]thiopyran-2-sulfonamide 7,7-dioxide monohydrochloride. Dorzolamide hydrochloride, USP is optically active. The specific rotation is

[α] 25°C (C=1,water) = ~ - 17°.
405 nm

Its empirical formula is C10H16N2O4S3.HCl and its structural formula is:

Dorzolamide hydrochloride, USP has a molecular weight of 360.9 and a melting point of about 264°C. It is a white to almost white crystalline powder, which is soluble in water and slightly soluble in methanol and very slightly soluble in anhydrous ethanol.

Dorzolamide Hydrochloride Ophthalmic Solution, USP is supplied as a sterile, isotonic, buffered, slightly viscous, aqueous solution of dorzolamide hydrochloride, USP. The pH of the solution is approximately 5.4 to 5.9, and the osmolarity is 260 to 330 mOsM. Each mL of Dorzolamide Hydrochloride Ophthalmic Solution, USP 2% contains 20 mg dorzolamide (22.3 mg of dorzolamide hydrochloride, USP). Inactive ingredients are hydroxyethyl cellulose, mannitol, sodium citrate dihydrate, sodium hydroxide (to adjust pH) and water for injection. Benzalkonium chloride 0.0075% is added as a preservative.

12 CLINICAL PHARMACOLOGY

12.1 Mechanism of Action

Carbonic anhydrase (CA) is an enzyme found in many tissues of the body including the eye. It catalyzes the reversible reaction involving the hydration of carbon dioxide and the dehydration of carbonic acid. In humans, carbonic anhydrase exists as a number of isoenzymes, the most active being carbonic anhydrase II (CA-II), found primarily in red blood cells (RBCs), but also in other tissues. Inhibition of carbonic anhydrase in the ciliary processes of the eye decreases aqueous humor secretion, presumably by slowing the formation of bicarbonate ions with subsequent reduction in sodium and fluid transport. The result is a reduction in intraocular pressure (IOP).

Dorzolamide Hydrochloride Ophthalmic Solution contains dorzolamide hydrochloride, an inhibitor of human carbonic anhydrase II. Following topical ocular administration, Dorzolamide Hydrochloride Ophthalmic Solution reduces elevated intraocular pressure. Elevated intraocular pressure is a major risk factor in the pathogenesis of optic nerve damage and glaucomatous visual field loss.

12.3 Pharmacokinetics

When topically applied, dorzolamide reaches the systemic circulation. To assess the potential for systemic carbonic anhydrase inhibition following topical administration, drug and metabolite concentrations in RBCs and plasma and carbonic anhydrase inhibition in RBCs were measured.

Dorzolamide accumulates in RBCs during chronic dosing as a result of binding to CA-II. The parent drug forms a single N-desethyl metabolite, which inhibits CA-II less potently than the parent drug but also inhibits CA-I. The metabolite also accumulates in RBCs where it binds primarily to CA-I. Plasma concentrations of dorzolamide and metabolite are generally below the assay limit of quantitation (15nM). Dorzolamide binds moderately to plasma proteins (approximately 33%).

Dorzolamide is primarily excreted unchanged in the urine; the metabolite also is excreted in urine. After dosing is stopped, dorzolamide washes out of RBCs nonlinearly, resulting in a rapid decline of drug concentration initially, followed by a slower elimination phase with a half-life of about four months.

To simulate the systemic exposure after long-term topical ocular administration, dorzolamide was given orally to eight healthy subjects for up to 20 weeks. The oral dose of 2 mg twice daily closely approximates the amount of drug delivered by topical ocular administration of dorzolamide 2% three times daily. Steady state was reached within 8 weeks. The inhibition of CA-II and total carbonic anhydrase activities was below the degree of inhibition anticipated to be necessary for a pharmacological effect on renal function and respiration in healthy individuals.

13 NONCLINICAL TOXICOLOGY

13.1 Carcinogenesis, Mutagenesis, Impairment of Fertility

In a two-year study of dorzolamide hydrochloride administered orally to male and female Sprague-Dawley rats, urinary bladder papillomas were seen in male rats in the highest dosage group of 20 mg/kg/day. Papillomas were not seen in rats given oral doses of 1 mg/kg/day. These doses represent estimated plasma Cmax levels in rats, 138 and 7 times higher than the lower limit of detection in human plasma following ocular administration, respectively.

No treatment-related tumors were seen in a 21-month study in female and male mice given oral doses up to 75 mg/kg/day. This dose represents an estimated plasma Cmax level in mice, 582 times higher than the lower limit of detection in human plasma following ocular administration.

The increased incidence of urinary bladder papillomas seen in the high-dose male rats is a class-effect of carbonic anhydrase inhibitors in rats. Rats are particularly prone to developing papillomas in response to foreign bodies, compounds causing crystalluria, and diverse sodium salts.

No changes in bladder urothelium were seen in dogs given oral dorzolamide hydrochloride for one year at 2 mg/kg/day or monkeys dosed topically to the eye for one year. An oral dose of 2 mg/kg/day in dogs represents an estimated plasma Cmax level, 137 times higher than the lower limit of detection in human plasma following ocular administration. The topical ophthalmic dose in monkeys was approximately equivalent to the human topical ophthalmic dose.

The following tests for mutagenic potential were negative: (1) in vivo (mouse) cytogenetic assay; (2) in vitro chromosomal aberration assay; (3) alkaline elution assay; (4) V-79 assay; and (5) Ames test.

In fertility studies of dorzolamide hydrochloride in rats, there were no adverse effects on the reproductive capacity of males or females at doses of 15 and 7.5 mg/kg/day, respectively. These doses represent estimated plasma Cmax levels in rats, 103 and 52 times higher than the lower limit of detection in human plasma following ocular administration, respectively.

14 CLINICAL STUDIES

The efficacy of Dorzolamide Hydrochloride Ophthalmic Solution was demonstrated in clinical studies in the treatment of elevated intraocular pressure in patients with glaucoma or ocular hypertension (baseline IOP ≥ 23 mmHg). The IOP-lowering effect of Dorzolamide Hydrochloride Ophthalmic Solution was approximately 3 to 5 mmHg throughout the day and this was consistent in clinical studies of up to one year duration.

The efficacy of Dorzolamide Hydrochloride Ophthalmic Solution when dosed less frequently than three times a day (alone or in combination with other products) has not been established.

In a one year clinical study, the effect of Dorzolamide Hydrochloride Ophthalmic Solution 2% three times daily on the corneal endothelium was compared to that of betaxolol ophthalmic solution twice daily and timolol maleate ophthalmic solution 0.5% twice daily. There were no statistically significant differences between groups in corneal endothelial cell counts or in corneal thickness measurements. There was a mean loss of approximately 4% in the endothelial cell counts for each group over the one year period.

16 HOW SUPPLIED/STORAGE AND HANDLING

Dorzolamide Hydrochloride Ophthalmic Solution, USP 2% is supplied in 10 mL ratchet modified screw neck white LDPE bottle with LDPE nozzle having white Opaque pump with a dip tube and Orange color ring modified HDPE screw cap as follows:

NDC | Dorzolamide Hydrochloride Ophthalmic Solution, USP 2% | Package Factor
25021-006-10 | 10 mL fill | 1 bottle per carton

Storage Conditions

Store at 15° to 30°C (59° to 86°F). After opening, Dorzolamide Hydrochloride Ophthalmic Solution, USP 2% can be used until the expiration date on the bottle.

Protect from light.

Sterile, Nonpyrogenic.
The container closure is not made with natural rubber latex.

17 PATIENT COUNSELING INFORMATION

Advise the patient to read the FDA-approved patient labeling (Instructions for Use).

Sulfonamide Reactions

Dorzolamide Hydrochloride Ophthalmic Solution is a sulfonamide and although administered topically is absorbed systemically. Therefore the same types of adverse reactions that are attributable to sulfonamides may occur with topical administration. Advise patients that if serious or unusual reactions including severe skin reactions or signs of hypersensitivity occur, they should discontinue the use of the product [see Warnings and Precautions (5.1)].

Intercurrent Ocular Conditions

Advise patients that if they have ocular surgery or develop an intercurrent ocular condition (e.g., trauma or infection), they should immediately seek their physician's advice concerning the continued use of the present multidose container.

Handling Ophthalmic Solutions

Instruct patients to avoid allowing the tip of the dispensing container to contact the eye or surrounding structures.

Instruct patients that ocular solutions, if handled improperly or if the tip of the dispensing container contacts the eye or surrounding structures, can become contaminated by common bacteria known to cause ocular infections. Serious damage to the eye and subsequent loss of vision may result from using contaminated solutions.

Concomitant Topical Ocular Therapy

If more than one topical ophthalmic drug is being used, the drugs should be administered at least five minutes apart.

Contact Lens Use

Advise patients that Dorzolamide Hydrochloride Ophthalmic Solution contains benzalkonium chloride which may be absorbed by soft contact lenses. Contact lenses should be removed prior to administration of the solution. Lenses may be reinserted 15 minutes following Dorzolamide Hydrochloride Ophthalmic Solution administration.

When to Seek Physician Advice

Advise patients that if they develop any ocular reactions, particularly conjunctivitis and lid reactions, they should discontinue use and seek their physician's advice.

sagent®

Mfd. for SAGENT Pharmaceuticals
Schaumburg, IL 60173 (USA)
Made in India
©2025 Sagent Pharmaceuticals

August 2025

PATIENT INFORMATION

INSTRUCTIONS FOR USE

Dorzolamide Hydrochloride Ophthalmic Solution, USP 2% (dor ZOL a mide)

Before using your dorzolamide hydrochloride ophthalmic solution

Before using your dorzolamide hydrochloride ophthalmic solution, for the first time, make sure the tamper evident ring of the bottle is unbroken. A gap between the bottle and the cap is normal for an unopened bottle. See Figure A.

Figure A

Step 1. Wash your hands.

Step 2. To open the bottle for the first time, hold the bottle upright, turn the cap counter-clockwise to break the tamper-evident ring. See Figure B.

Figure B

Step 3. Unscrew the cap by turning further in the direction as shown in the Figure C until the cap comes-off. The tamper-evident ring will remain in the bottle neck.

Figure C

Giving your dorzolamide hydrochloride ophthalmic solution drops.

Step 4. Tilt your head back and pull your lower eyelid down slightly to form a pocket between your eyelid and your eye. See Figure D.

Figure D

Step 5. Hold the dorzolamide hydrochloride ophthalmic solution, USP 2% bottle upside down. Place tip as close as possible to the lower eyelid without touching the tip to the eye, and gently squeeze until a single drop is placed in your eye. Do not touch your eye or eyelid with the dropper tip. See Figure E.

Figure E

Step 6. The dispenser tip is designed to provide a pre-measured drop; therefore, do NOT enlarge the hole of the dispenser tip.

Step 7. If your doctor has told you to use Dorzolamide Hydrochloride Ophthalmic Solution, USP 2% in both eyes, repeat steps 4 and 5.

After using your dorzolamide hydrochloride ophthalmic solution

Step 8. Replace the cap by turning it until it is firmly touching your bottle. (see Figure F).

Figure F

After you have used all of your dorzolamide hydrochloride ophthalmic solution, USP 2% doses, there will be some dorzolamide hydrochloride ophthalmic solution, USP 2% medicine left in the dispenser. Do not try to remove the extra medicine from the dorzolamide hydrochloride ophthalmic solution, USP 2% dispenser. Throw away your dorzolamide hydrochloride ophthalmic solution, USP 2% dispenser in your household trash.

How should I store dorzolamide hydrochloride ophthalmic solution?

- Store dorzolamide hydrochloride ophthalmic solution between 15° to 30°C (59° to 86°F)
- Protect from light
- After opening, dorzolamide hydrochloride ophthalmic solution can be used until the expiration date on the bottle.
- Safely throw away medicine that is out of date or no longer needed.

KEEP DORZOLAMIDE HYDROCHLORIDE OPHTHALMIC SOLUTION AND ALL MEDICINES OUT OF THE REACH OF CHILDREN.

Important information about using dorzolamide hydrochloride ophthalmic solution

- If you have any eye or skin reactions, especially conjunctivitis or eyelid reactions to dorzolamide hydrochloride ophthalmic solution, stop using it and call your doctor right away.
- If you have eye surgery or have a problem such as trauma or infection of your eye while using dorzolamide hydrochloride ophthalmic solution, call your doctor right away.
- If you do not handle eye medicines the right way the medicine can become contaminated. If the tip of the dispenser touches your eye or areas around your eye, the tip can become contaminated with bacteria which can cause an eye infection and other serious problems including loss of eyesight.
- If you use other eye medicines dropped onto the eye like dorzolamide hydrochloride ophthalmic solution, use the medicines at least 5 minutes before or after you use dorzolamide hydrochloride ophthalmic solution.
- Dorzolamide hydrochloride ophthalmic solution contains benzalkonium chloride which may be absorbed by soft contact lenses. If you wear contact lenses, remove them before you use your dorzolamide hydrochloride ophthalmic solution. You can place your contact lenses back into your eyes 15 minutes after using your dorzolamide hydrochloride ophthalmic solution.

This Instructions for Use has been approved by the U.S. Food and Drug Administration.

sagent®
Mfd. for SAGENT Pharmaceuticals
Schaumburg, IL 60173 (USA)
Made in India
©2025 Sagent Pharmaceuticals

August 2025

PACKAGE LABEL – PRINCIPAL DISPLAY PANEL – Bottle Label

NDC 25021-006-10

Rx only

Dorzolamide Hydrochloride Ophthalmic Solution, USP

2% 10 mL

Sterile

For Topical Application in the Eye